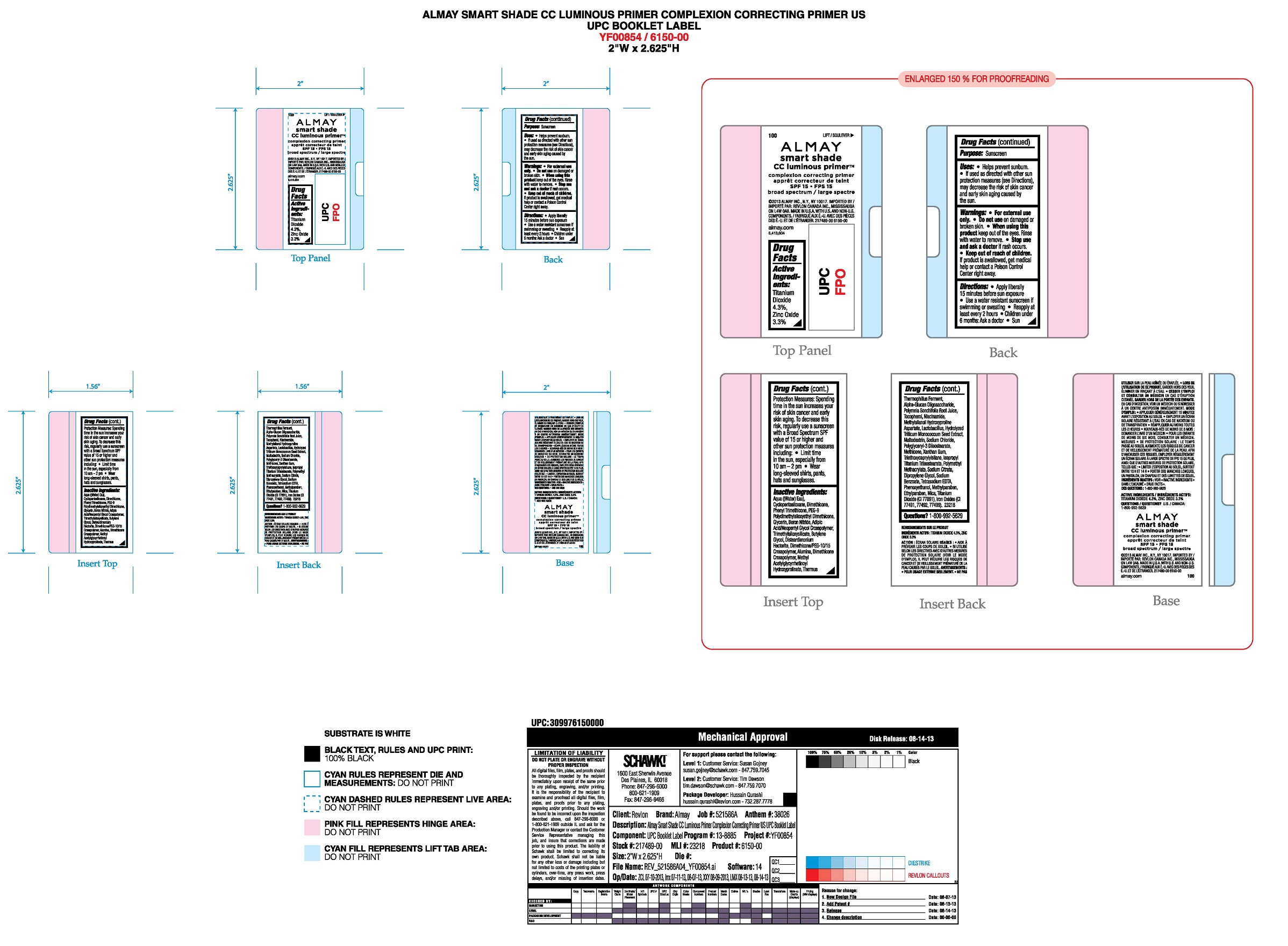 DRUG LABEL: Almay Age Smart Shade CC Luminous Primer SPF 15
NDC: 0311-0706 | Form: LIQUID
Manufacturer: Almay, Inc.
Category: otc | Type: HUMAN OTC DRUG LABEL
Date: 20241224

ACTIVE INGREDIENTS: ZINC OXIDE 3.3 mg/1 mL; TITANIUM DIOXIDE 4.3 mg/1 mL
INACTIVE INGREDIENTS: WATER; DIMETHICONE; PHENYL TRIMETHICONE; METHICONE (20 CST); ALUMINUM OXIDE; XANTHAN GUM; NIACINAMIDE; TRIMETHYLSILOXYSILICATE (M/Q 0.8-1.0); CYCLOMETHICONE 5; PEG-9 POLYDIMETHYLSILOXYETHYL DIMETHICONE; BORON NITRIDE; DISTEARDIMONIUM HECTORITE; PHENOXYETHANOL; SODIUM CHLORIDE; POTASSIUM SORBATE; TRIETHOXYCAPRYLYLSILANE; TOCOPHEROL; EDETATE SODIUM; GLYCERIN; POLYGLYCERYL-3 DIISOSTEARATE; DIPROPYLENE GLYCOL; SODIUM CITRATE, UNSPECIFIED FORM; MICA; FERRIC OXIDE RED; BUTYLENE GLYCOL; THERMUS THERMOPHILUS LYSATE; .ALPHA.-GLUCAN OLIGOSACCHARIDE; LACTOBACILLUS ACIDOPHILUS; MALTODEXTRIN; ISOPROPYL TITANIUM TRIISOSTEARATE; POLY(METHYL METHACRYLATE; 450000 MW); SODIUM BENZOATE; METHYLPARABEN; ETHYLPARABEN

Almay Age Smart Shade CC Luminous Primer SPF 15

Active Ingredients:

Zinc Oxide: 3.3%

Titanium Dioxide 4.3%

Purpose

Sunscreen

Uses:

•Helps prevent sunburn
•If used as directed with other sun protection measures (see Directions), decreases the risk of skin cancer and early skin aging caused by the sun

Warnings:

•For external use only
•Do notuse on damaged or broken skin
•When using this product: Keep out of eyes. Rinse with water to remove.
•Stop use and ask a doctor if a rash occurs
•Keep out of reach of children. If product is swallowed, get medical help or contact a Poison Control center right away

Directions

•Apply liberally 15 minutes before sun exposure
•Use a water resistant sunscreen if swimming or sweating
•Reapply at least every 2 hours
•Children under 6 months: Ask a doctor.

Sun Protection Measures

Spending time in the sun increases your risk of skin cancer and early skin aging. To decrease this risk, regularly use a sunscreen with a Broad Spectrum SPF value of 15 or higher and other sun protection measures including:
•Limit time in the sun, especially from 10 am - 2 pm
•Wear long-sleeved shirts, pants, hats and sunglasses.

Inactive Ingredients

Aqua ((Water) Eau), Cyclopentasiloxane, Dimethicone, Phenyl Trimethicone, PEG-9 Polydimethylsiloxyethyl Dimethicone, Glycerin, Boron Nitride, Adipic Acid/Neopentyl Glycol Crosspolymer, Trimethylsiloxysilicate, Butylene Glycol, Disteardimonium Hectorite, Dimethicone/PEG-10/15 Crosspolymer, Alumina, Dimethicone Crosspolymer, Methyl Acetylglycyrrhetinoyl Hydroxyprolinate, Thermus Thermophillus Ferment, Alpha-Glucan Oligosaccharide, Polymnia Sonchifolia Root Juice, Tocopherol, Niacinamide, Methylsilanol Hydroxyproline Aspartate, Lactobacillus, Hydrolyzed Triticum Monococcum Seed Extract, Maltodextrin, Sodium Chloride, Polyglyceryl-3 Diisostearate, Methicone, Xanthan Gum, Triethoxycaprylylsilane, Isopropyl Titanium Triisostearate, Polymethyl Methacrylate, Sodium Citrate, Dipropylene Glycol, Sodium Benzoate, Tetrasodium EDTA, Phenoxyethanol, Methylparaben, Ethylparaben, Mica, Titanium Dioxide (CI 77891), Iron Oxides (CI 77491, 77492, 77499)

Directions

•Apply liberally 15 minutes before sun exposure
•Use a water resistant sunscreen if swimming or sweating
•Reapply at least every 2 hours
•Children under 6 months: Ask a doctor.

Warnings

•Keep out of reach of children. If product is swallowed, get medical help or contact a Poison Control center right away

Principal Display Panel

Almay

Smart Shade CC Luminous Primer

Broad Spectrum

SPF 15

1.0 fL. OZ/30 mL